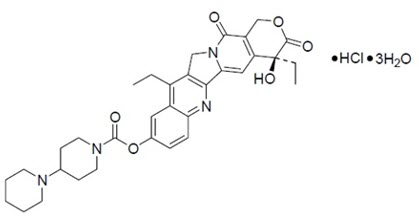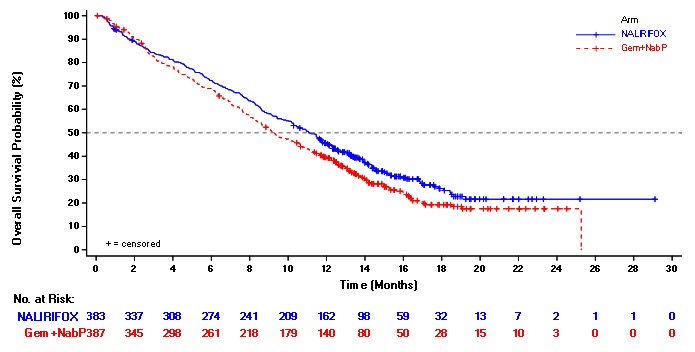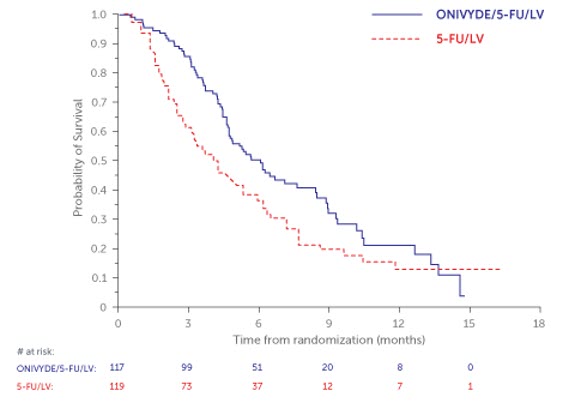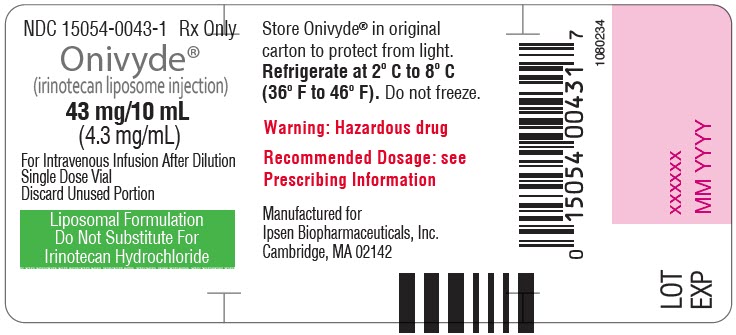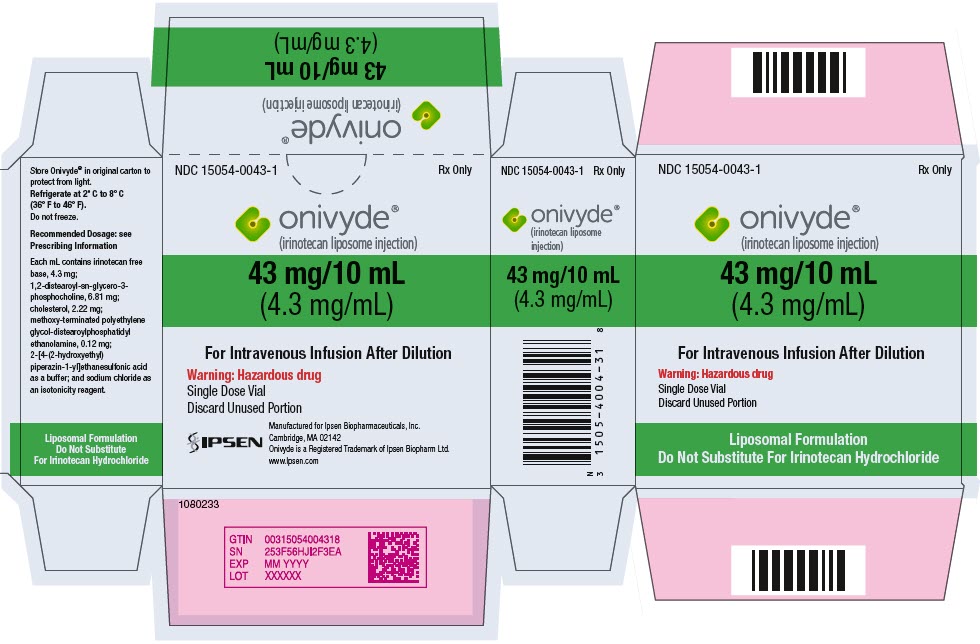 DRUG LABEL: Onivyde
NDC: 15054-0043 | Form: INJECTION, POWDER, FOR SOLUTION
Manufacturer: Ipsen Biopharmaceuticals, Inc.
Category: prescription | Type: HUMAN PRESCRIPTION DRUG LABEL
Date: 20250303

ACTIVE INGREDIENTS: IRINOTECAN HYDROCHLORIDE 4.3 mg/1 mL
INACTIVE INGREDIENTS: 1,2-DISTEAROYL-SN-GLYCERO-3-PHOSPHOCHOLINE; CHOLESTEROL; SODIUM N-(CARBONYL-METHOXYPOLYETHYLENE GLYCOL 2000)-1,2-DISTEAROYL-SN-GLYCERO-3-PHOSPHOETHANOLAMINE; HYDROXYETHYLPIPERAZINE ETHANE SULFONIC ACID; SODIUM CHLORIDE

HIGHLIGHTS OF PRESCRIBING INFORMATION

These highlights do not include all the information needed to use ONIVYDE safely and effectively. See full prescribing information for ONIVYDE
ONIVYDE® (irinotecan liposome injection), for intravenous use
Initial U.S. Approval: 1996

WARNING: SEVERE NEUTROPENIA AND SEVERE DIARRHEA

See full prescribing information for complete boxed warning

Neutropenia

- Severe or life-threatening neutropenia , including fatal neutropenic sepsis and fatal neutropenic fever, has occurred in patients receiving ONIVYDE in combination with oxaliplatin, fluorouracil and leucovorin and in combination with fluorouracil and leucovorin. Withhold ONIVYDE for absolute neutrophil count below 1500/mm^3 or neutropenic fever. Monitor blood cell counts periodically during treatment (2.2), (5.1).

Diarrhea

- Severe and life-threatening diarrhea has occurred in patients receiving ONIVYDE in combination with oxaliplatin, fluorouracil and leucovorin and in combination with fluorouracil and leucovorin. Do not administer ONIVYDE to patients with bowel obstruction. Withhold ONIVYDE for diarrhea of Grade 2-4 severity. Administer loperamide for late diarrhea of any severity. Administer atropine, if not contraindicated, for early diarrhea of any severity (2.2), (5.2).

RECENT MAJOR CHANGES

Indications and Usage (1) | 02/2024
Warnings and Precautions (5.1, 5.2) | 02/2024
Warnings and Precautions (5.3) | 12/2024

1 INDICATIONS AND USAGE

ONIVYDE is a topoisomerase inhibitor indicated:

- in combination with oxaliplatin, fluorouracil and leucovorin, for the first-line treatment of adult patients with metastatic pancreatic adenocarcinoma, (1)
- in combination with fluorouracil and leucovorin, for the treatment of adult patients with metastatic pancreatic adenocarcinoma after disease progression following gemcitabine-based therapy. (1)

Limitation of Use: ONIVYDE is not indicated as a single agent for the treatment of patients with metastatic pancreatic adenocarcinoma. (1)

2 DOSAGE AND ADMINISTRATION

- Do not substitute ONIVYDE for other drugs containing irinotecan HCl. (2.1)
- ONIVYDE in combination with oxaliplatin, fluorouracil and leucovorin:
  - Recommended dose of ONIVYDE is 50 mg/m^2 intravenous infusion over 90 minutes every two weeks. (2.2)
  - Recommended starting dose of ONIVYDE in patients homozygous for UGT1A1*28 is 50 mg/m^2 every two weeks. (2.2)
  - There is no recommended dose of ONIVYDE for patients with serum bilirubin above the upper limit of normal. (2.2)
- ONIVYDE in combination with fluorouracil and leucovorin:
  - Recommended dose of ONIVYDE is 70 mg/m^2 intravenous infusion over 90 minutes every two weeks. (2.2)
  - Recommended starting dose of ONIVYDE in patients homozygous for UGT1A1*28 is 50 mg/m^2 every two weeks. (2.2)
  - There is no recommended dose of ONIVYDE for patients with serum bilirubin above the upper limit of normal. (2.2)
- Premedicate with a corticosteroid and an anti-emetic 30 minutes prior to ONIVYDE. (2.2)

3 DOSAGE FORMS AND STRENGTHS

Injection: 43 mg/10 mL (4.3 mg/mL) single dose vial (3)

4 CONTRAINDICATIONS

Severe hypersensitivity reaction to ONIVYDE or irinotecan HCl. (4, 5.4)

5 WARNINGS AND PRECAUTIONS

- Interstitial lung disease (ILD): Fatal ILD has occurred in patients receiving irinotecan including ONIVYDE. Discontinue ONIVYDE if ILD is diagnosed. (5.3)
- Severe hypersensitivity reaction: Permanently discontinue ONIVYDE for severe hypersensitivity reactions. (5.4, 4)
- Embryo-fetal toxicity: Can cause fetal harm. Advise females of reproductive potential of the potential risk to a fetus and to use effective contraception. (5.5, 8.1, 8.3)

6 ADVERSE REACTIONS

The most common adverse reactions (reported in ≥ 20% of patients) were for:

- ONIVYDE in combination with oxaliplatin, fluorouracil and leucovorin: diarrhea, fatigue, nausea, vomiting, decreased appetite, abdominal pain, mucosal inflammation, constipation, and decreased weight. The most common laboratory abnormalities (≥ 10% Grade 3 or 4) were decreased neutrophils, decreased potassium, decreased lymphocytes, and decreased hemoglobin. (6.1)
- ONIVYDE in combination with fluorouracil and leucovorin: diarrhea, fatigue/asthenia, vomiting, nausea, decreased appetite, stomatitis, and pyrexia. The most common laboratory abnormalities (≥ 10% Grade 3 or 4) were lymphopenia and neutropenia. (6.1)

To report SUSPECTED ADVERSE REACTIONS, contact Ipsen Biopharmaceuticals, Inc.at 1-855-463-5127 or FDA at 1-800-FDA-1088 or www.fda.gov/medwatch.

7 DRUG INTERACTIONS

- Strong CYP3A4 Inducers: Avoid the use of strong CYP3A4 inducers if possible. Substitute non-enzyme inducing therapies at least 2 weeks prior to initiation of ONIVYDE. (7.1)
- Strong CYP3A4 Inhibitors: Avoid the use of strong CYP3A4 or UGT1A1 inhibitors, if possible; discontinue strong CYP3A4 inhibitors at least 1 week prior to starting therapy. (7.2)

8 USE IN SPECIFIC POPULATIONS

- Lactation: Do not breastfeed. (8.2)

FULL PRESCRIBING INFORMATION

WARNING: SEVERE NEUTROPENIA AND SEVERE DIARRHEA

Neutropenia

- Severe and life-threatening neutropenia, including fatal neutropenic sepsis and fatal neutropenic fever, has occurred in patients receiving ONIVYDE in combination with oxaliplatin, fluorouracil and leucovorin and in combination with fluorouracil and leucovorin. Withhold ONIVYDE for absolute neutrophil count below 1500/mm^3 or neutropenic fever. Monitor blood cell counts periodically during treatment [see Dosage and Administration (2.2) and Warnings and Precautions (5.1)].

Diarrhea

- Severe and life-threatening diarrhea has occurred in patients receiving ONIVYDE in combination with oxaliplatin, fluorouracil and leucovorin and in combination with fluorouracil and leucovorin. Do not administer ONIVYDE to patients with bowel obstruction. Withhold ONIVYDE for diarrhea of Grade 2-4 severity. Administer loperamide for late diarrhea of any severity. Administer atropine, if not contraindicated, for early diarrhea of any severity [see Dosage and Administration (2.2) and Warnings and Precautions (5.2)].

1 INDICATIONS AND USAGE

- ONIVYDE is indicated, in combination with oxaliplatin, fluorouracil and leucovorin for the first-line treatment of adult patients with metastatic pancreatic adenocarcinoma.
- ONIVYDE is indicated, in combination with fluorouracil and leucovorin, for the treatment of adult patients with metastatic pancreatic adenocarcinoma after disease progression following gemcitabine-based therapy.

Limitations of Use: ONIVYDE is not indicated as a single agent for the treatment of patients with metastatic pancreatic adenocarcinoma. [see Clinical Studies (14)].

2 DOSAGE AND ADMINISTRATION

2.1 Important Use Information

DO NOT SUBSTITUTE ONIVYDE for other drugs containing irinotecan HCl.

2.2 Recommended Dosage

In combination with oxaliplatin, fluorouracil and leucovorin for the first-line treatment of patients with metastatic pancreatic adenocarcinoma

Administer ONIVYDE prior to oxaliplatin, fluorouracil and leucovorin [see Clinical Studies (14)].

- The recommended dosage of ONIVYDE regardless of UGT1A1*28 allele genotype is 50 mg/m^2 administered by intravenous infusion over 90 minutes every 2 weeks.
- There is no recommended dosage of ONIVYDE for patients with serum bilirubin above the upper limit of normal [see Adverse Reactions (6.1) and Clinical Studies (14)].

In combination with fluorouracil and leucovorin for the treatment of patients with metastatic pancreatic adenocarcinoma after disease progression following gemcitabine-based therapy

Administer ONIVYDE prior to fluorouracil and leucovorin [see Clinical Studies (14)].

- The recommended dosage of ONIVYDE is 70 mg/m^2 administered by intravenous infusion over 90 minutes every 2 weeks.
- The recommended starting dose of ONIVYDE in patients known to be homozygous for the UGT1A1*28 allele is 50 mg/m^2 administered by intravenous infusion over 90 minutes. Increase the dose of ONIVYDE to 70 mg/m^2 as tolerated in subsequent cycles.
- There is no recommended dosage of ONIVYDE for patients with serum bilirubin above the upper limit of normal [see Adverse Reactions (6.1) and Clinical Studies (14)].

Premedication

Administer a corticosteroid and an anti-emetic 30 minutes prior to each ONIVYDE infusion.

2.3 Dosage Modifications for Adverse Reactions

Recommended dosage modifications for ONIVYDE are in Table 1 and Table 2.

Table 1 Recommended Dosage Modifications for ONIVYDE in combination with oxaliplatin, fluorouracil and leucovorin
Toxicity [Toxicity grading per NCI CTCAE v5.0.] | Occurrence | ONIVYDE adjustment in patients receiving 50mg/m^2
Grade 3 or 4 Adverse reactions [No dosage modification is necessary for asthenia, alopecia and Grade 3 anorexia.] | Withhold ONIVYDE Upon recovery to ≤ Grade 1 [Do not resume until the absolute neutrophil count is ≥2000/mm^3 (2×10^9/L) and the platelet count is ≥100,000/mm^3 (100×10^9/L).] , [For Grade ≥3 nausea and vomiting, reduce dose only if occurs despite optimal anti-emetic therapy.] , [Refer to the Full Prescribing Information of fluorouracil and oxaliplatin. When ONIVYDE dose is reduced for adverse reactions, reduce fluorouracil (FU) and oxaliplatin doses: for first occurrence, reduce dose to 80% of original dose; for second occurrence, reduce dose to 65% of original dose; for third occurrence, reduce dose to 50% of original dose; discontinue therapy for fourth occurrence. Oxaliplatin may be discontinued if not well tolerated and treatment with ONIVYDE + FU/LV can continue. Maintain original dose level of leucovorin for first, second and third occurrence of toxicity.] , resume ONIVYDE at:
Grade 3 or 4 Adverse reactions [No dosage modification is necessary for asthenia, alopecia and Grade 3 anorexia.] | First | 40 mg/m^2
Grade 3 or 4 Adverse reactions [No dosage modification is necessary for asthenia, alopecia and Grade 3 anorexia.] | Second | 32.5 mg/m^2
Grade 3 or 4 Adverse reactions [No dosage modification is necessary for asthenia, alopecia and Grade 3 anorexia.] | Third | 25 mg/m^2
Grade 3 or 4 Adverse reactions [No dosage modification is necessary for asthenia, alopecia and Grade 3 anorexia.] | Fourth | Discontinue ONIVYDE
Grade 3 or 4 Hand foot syndrome | First | Discontinue ONIVYDE
Any grade neurocerebellar toxicity | First | Discontinue ONIVYDE
Grade ≥ 2 cardiac toxicity | First | Discontinue ONIVYDE
Interstitial lung disease | First | Discontinue ONIVYDE
Anaphylactic reaction | First | Discontinue ONIVYDE

Table 2 Recommended Dosage Modifications for ONIVYDE in combination with fluorouracil and leucovorin
Toxicity NCI CTCAE v4.0 [NCI CTCAE v 4.0=National Cancer Institute Common Toxicity Criteria for Adverse Events version 4.0] | Occurrence | ONIVYDE adjustment in patients receiving 70 mg/m^2 | Patients homozygous for UGT1A1*28 without previous increase to 70 mg/m^2
Grade 3 or 4 adverse reactions | Withhold ONIVYDE. Upon recovery to ≤ Grade 1, resume ONIVYDE at:
Grade 3 or 4 adverse reactions | First | 50 mg/m^2 | 43 mg/m^2
Grade 3 or 4 adverse reactions | Second | 43 mg/m^2 | 35 mg/m^2
Grade 3 or 4 adverse reactions | Third | Discontinue ONIVYDE | Discontinue ONIVYDE
Interstitial Lung Disease | First | Discontinue ONIVYDE | Discontinue ONIVYDE
Anaphylactic Reaction | First | Discontinue ONIVYDE | Discontinue ONIVYDE

For recommended dose modifications of fluorouracil (FU) or leucovorin (LV), refer to the Full Prescribing Information; refer to Clinical Studies (14).

2.4 Preparation and Administration

ONIVYDE is a hazardous drug. Follow applicable special handling and disposal procedures.^1

Preparation

- Withdraw the calculated volume of ONIVYDE from the vial. Dilute ONIVYDE in 500 mL 5% Dextrose Injection, USP or 0.9% Sodium Chloride Injection, USP and mix diluted solution by gentle inversion. Discard vials with any unused portion.
- Protect diluted solution from light.
- Administer diluted solution within 4 hours of preparation when stored at room temperature or within 24 hours of preparation when stored under refrigerated conditions [2ºC to 8ºC (36ºF to 46ºF)]. Allow diluted solution to come to room temperature prior to administration.
- Do NOT freeze.

Administration

- Infuse diluted solution intravenously over 90 minutes.

3 DOSAGE FORMS AND STRENGTHS

Injection: 43 mg/10 mL irinotecan free base as a white to slightly yellow, opaque, liposomal dispersion in a single-dose vial.

4 CONTRAINDICATIONS

ONIVYDE is contraindicated in patients who have experienced a severe hypersensitivity reaction or anaphylaxis to ONIVYDE or irinotecan HCl. [see Warnings and Precautions (5.4), Adverse Reactions (6.2)].

5 WARNINGS AND PRECAUTIONS

5.1 Severe Neutropenia

ONIVYDE can cause severe or life-threatening neutropenia and fatal neutropenic sepsis.

In NAPOLI 3, Grade 3 and 4 neutropenia occurred in 26% of patients receiving ONIVYDE in combination with oxaliplatin, fluorouracil, and leucovorin (NALIRIFOX) and fatal neutropenic fever in 0.3% of patients [see Adverse Reactions (6.1)]. In NAPOLI-1, Grade 3 and 4 neutropenia occurred in 20% of patients receiving ONIVYDE in combination with fluorouracil and leucovorin (ONIVYDE/FU/LV). Neutropenic sepsis occurred in 3% and fatal neutropenic sepsis in 0.8% [see Adverse Reactions (6.1)].

In NAPOLI 3, the incidence of Grade 3 or 4 neutropenia was similar among Asian patients [6 of 20 (30%)] compared to White patients [76 of 289 (26%)] receiving ONIVYDE in combination with oxaliplatin, fluorouracil, and leucovorin. Neutropenic fever was reported in 5% of Asian patients (1 of 20) compared to 2.3% of White patients (7 of 306). In NAPOLI-1, the incidence of Grade 3 or 4 neutropenia was higher among Asian patients [18 of 33 (55%)] compared to White patients [13 of 73 (18%)] receiving ONIVYDE/FU/LV. Neutropenic fever/neutropenic sepsis was reported in 6% of Asian patients compared to 1% of White patients [see Clinical Pharmacology (12.3)].

Monitor complete blood cell counts on Days 1 and 8 of every cycle and more frequently if clinically indicated. Withhold ONIVYDE if the absolute neutrophil count (ANC) is below 1500/mm^3 or if neutropenic fever occurs. Resume ONIVYDE when the ANC is 1500/mm^3 or above. Reduce ONIVYDE dose for Grade 3-4 neutropenia or neutropenic fever following recovery in subsequent cycles [see Dosage and Administration (2.2)].

5.2 Severe Diarrhea

ONIVYDE can cause severe and life-threatening diarrhea. Do not administer ONIVYDE to patients with a bowel obstruction. Severe or life-threatening diarrhea can follow one of two patterns: late onset diarrhea (onset more than 24 hours following chemotherapy) and early onset diarrhea (onset within 24 hours of chemotherapy, sometimes occurring with other symptoms of cholinergic reaction) [see Adverse Reactions (6.1)]. An individual patient may experience both early and late-onset diarrhea.

In NAPOLI 3, Grade 3 and 4 diarrhea (early and late-onset) occurred in 20% receiving ONIVYDE in combination with oxaliplatin, fluorouracil, and leucovorin (NALIRIFOX). In NAPOLI-1, Grade 3 or 4 diarrhea occurred in 13% receiving ONIVYDE/FU/LV. The incidence of Grade 3 or 4 late onset diarrhea was 9% in patients receiving ONIVYDE/FU/LV. The incidence of Grade 3 or 4 early onset diarrhea was 3% in patients receiving ONIVYDE/FU/LV. Of patients receiving ONIVYDE/FU/LV in NAPOLI-1, 34% received loperamide for late-onset diarrhea and 26% received atropine for early-onset diarrhea.

To reduce the risk of severe diarrhea, patients should stop lactose-containing products, eat a low-fat diet and maintain hydration during treatment with ONIVYDE. Withhold ONIVYDE for Grade 2-4 diarrhea. Administer intravenous or subcutaneous atropine 0.25 to 1 mg (unless clinically contraindicated) for early onset diarrhea of any severity. Initiate loperamide for late onset diarrhea of any severity. Local institutional guidelines should be followed for the treatment of diarrhea that does not improve within 48 hours and may include the addition of diphenoxylate hydrochloride plus atropine sulfate or octreotide. Following recovery to Grade 1 diarrhea, resume ONIVYDE at a reduced dose [see Dosage and Administration (2.3)].

5.3 Interstitial Lung Disease

ONIVYDE can cause severe and fatal interstitial lung disease (ILD), including pneumonitis. Postmarketing cases of severe and fatal ILD have been reported with ONIVYDE. Risk factors include pre-existing lung disease, use of pneumotoxic medicinal products, colony stimulating factors or having previously received radiation therapy. Patients with risk factors should be closely monitored for respiratory symptoms before and during ONIVYDE therapy. Withhold ONIVYDE in patients with new or progressive dyspnea, cough, and fever, pending diagnostic evaluation. Discontinue ONIVYDE in patients with a confirmed diagnosis of ILD.

5.4 Severe Hypersensitivity Reaction

Irinotecan including ONIVYDE can cause severe hypersensitivity reactions, including anaphylactic reactions. Permanently discontinue ONIVYDE in patients who experience a severe hypersensitivity reaction [see Contraindications (4), Adverse reactions (6.2)].

5.5 Embryo-Fetal Toxicity

Based on animal data with irinotecan HCl and the mechanism of action of ONIVYDE, ONIVYDE can cause fetal harm when administered to a pregnant woman. Embryotoxicity and teratogenicity were observed following treatment with irinotecan HCl, at doses resulting in irinotecan exposures lower than those achieved with ONIVYDE 70 mg/m^2 in humans, administered to pregnant rats and rabbits during organogenesis. Advise pregnant women of the potential risk to a fetus. Advise females of reproductive potential to use effective contraception during treatment with ONIVYDE and for seven months following the last dose [see Use in Specific Populations (8.1, 8.3), Clinical Pharmacology (12.1)].

6 ADVERSE REACTIONS

The following adverse drug reactions are discussed in greater detail in other sections of the label:

- Severe Neutropenia [see Warnings and Precautions (5.1)]
- Severe Diarrhea [see Warnings and Precautions (5.2)]
- Interstitial Lung Disease [see Warnings and Precautions (5.3)]
- Severe Hypersensitivity Reactions [see Warnings and Precautions (5.4)]

6.1 Clinical Trials Experience

Because clinical trials are conducted under widely varying conditions, adverse reaction rates observed in clinical trials of ONIVYDE cannot be directly compared to rates in clinical trials of other drugs and may not reflect the rates observed in practice.

Pancreatic Adenocarcinoma

In Combination with Oxaliplatin, Fluorouracil and Leucovorin for First-Line Treatment

The safety of ONIVYDE in patients with metastatic pancreatic adenocarcinoma who had not previously received chemotherapy was evaluated in NAPOLI 3 [see Clinical Studies (14)]. Patients received ONIVYDE 50 mg/m^2 in combination with oxaliplatin 60 mg/m^2, leucovorin 400 mg/m^2 and fluorouracil 2400 mg/m^2 over 46 hours every 2 weeks (NALIRIFOX; N=383) or nab-paclitaxel 125 mg/m^2 over 35 minutes and gemcitabine 1000 mg/m^2 over 30 minutes on Day 1, 8 and 15 of each 28-day cycle (Gem+NabP; N=387). The median duration of exposure to ONIVYDE in combination with oxaliplatin, fluorouracil, and leucovorin was 24 weeks (range: 0 to 101 weeks).

Serious adverse reactions occurred in 54% of patients who received ONIVYDE in combination with oxaliplatin, fluorouracil and leucovorin. Serious adverse reactions in ≥2% of patients included infections including COVID-19 (14%), diarrhea (9%), vomiting (6%), nausea (4.9%), fatigue (3.8%), embolism (3.5%), gastrointestinal tract stenosis or obstruction (3.5%), hemorrhage (3%), abdominal pain (2.7%), cerebrovascular accident (2.7%), dehydration (2.7%), liver function test abnormalities (2.2%), and pyrexia (2.2%). Fatal adverse reactions occurred in 6% of patients who received ONIVYDE in combination with oxaliplatin, fluorouracil and leucovorin including cerebrovascular accident (1.1%), hemorrhage (0.5%), pneumonia (0.5%), sepsis (0.5%) and sudden death (0.5%).

Permanent discontinuation of ONIVYDE due to an adverse reaction occurred in 17% of patients. Adverse reactions which resulted in permanent discontinuation of ONIVYDE in ≥1% of patients included neutropenia, thrombocytopenia, diarrhea, fatigue, infections and cerebrovascular accident.

Dosage reduction of ONIVYDE due to an adverse reaction occurred in 52% of patients. Adverse reactions which required dosage reduction in ≥1% of patients included anemia, decreased appetite, diarrhea, fatigue, febrile neutropenia, hypokalemia, liver function test abnormalities, nausea, mucosal inflammation, neutropenia, peripheral neuropathy, vomiting, thrombocytopenia and weight decreased.

Dosage interruptions of ONIVYDE due to an adverse reaction occurred in 1.9% of patients. Adverse reactions which required dosage interruption in ≥0.5% of patients included hypersensitivity and infusion related reaction.

The most common adverse reactions (≥20% with a difference between arms of ≥ 5% for all grades or ≥ 2% for Grades 3 or 4 compared to Gem+NabP) of ONIVYDE in combination with oxaliplatin, fluorouracil, and leucovorin were diarrhea, fatigue, nausea, vomiting, decreased appetite, abdominal pain, mucosal inflammation, constipation and decreased weight. The most common laboratory abnormalities (≥10% Grade 3 or 4) were decreased neutrophils, decreased potassium, decreased lymphocyte and decreased hemoglobin.

Table 3 and 4 summarize the adverse reactions and laboratory abnormalities, respectively, in the NAPOLI 3 study.

Table 3 Adverse Reactions [NCI CTCAE v5.0] (≥ 20%) in Patients with Metastatic Pancreatic Adenocarcinoma who Received NALIRIFOX [NALIRIFOX=ONIVYDE+oxaliplatin/5-fluorouracil/leucovorin; Gem+NabP=gemcitabine+nab-paclitaxel] with a Difference Between Arms of ≥5% for All Grades or ≥ 2% for Grades 3 and 4 versus Gem+NabP in NAPOLI 3
Adverse Reaction | NALIRIFOX N=370 |  | Gem+NabP N=379
Adverse Reaction | All Grades (%) | Grade 3 or4 (%) | All Grades (%) | Grade 3 or4 (%)
Gastrointestinal disorders
Diarrhea [Includes multiple related terms] | 72 | 22 | 37 | 5
Nausea | 59 | 12 | 43 | 2.6
Vomiting | 40 | 7 | 27 | 2.1
Abdominal pain | 35 | 4.3 | 25 | 4.7
Constipation | 25 | 0.8 | 30 | 2.1
General disorders and administration site condition
Fatigue | 62 | 15 | 63 | 10
Mucosal inflammation | 28 | 3.8 | 17 | 0.8
Peripheral edema | 16 | 0.3 | 34 | 2.4
Pyrexia | 11 | 0.8 | 24 | 1.6
Investigations
Weight decreased | 22 | 3 | 9 | 0.3
Metabolism and nutrition disorders
Decreased appetite | 37 | 9 | 28 | 2.6
Dehydration | 11 | 3.2 | 9 | 1.1
Skin and subcutaneous tissue disorders
Alopecia | 14 | 0 | 31 | 0.5
Rash | 11 | 0.3 | 22 | 1.6
Nail disorder | 0.3 | 0 | 7 | 0.3
Vascular disorders
Hemorrhage | 11 | 2.4 | 18 | 3.4
Embolism | 11 | 7 | 11 | 5
Respiratory, thoracic and mediastinal disorders
Dyspnea | 8 | 0.5 | 13 | 2.1
Musculoskeletal and connective tissue disorders
Musculoskeletal pain | 18 | 1.6 | 27 | 1.1
Infections and infestations
Pneumonia | 2.4 | 1.6 | 6 | 4
Sepsis | 1.6 | 1.1 | 6 | 3.4

Table 4 Laboratory Abnormalities in Patients with Metastatic Pancreatic Adenocarcinoma who Received NALIRIFOX [NALIRIFOX=ONIVYDE+oxaliplatin/5-fluorouracil/leucovorin ; Gem+NabP=gemcitabine+nab-paclitaxel] with a difference between arms of ≥ 5% versus Gem+NabP in NAPOLI 3 [Each test incidence is based on the number of patients who had both baseline and at least one on-study laboratory measurement available: NALIRIFOX (range: 294 to 351 patients) and Gem+NabP (range: 303 to 373 patients).]
Laboratory abnormality | NALIRIFOX |  | Gem-NabP
Laboratory abnormality | All Grades (%) | Grade 3- or 4 (%) | All Grades (%) | Grade 3 or4 (%)
Hematology
Hemoglobin decreased | 91 | 10 | 96 | 15
Lymphocytes decreased | 64 | 11 | 76 | 19
Leukocytes decreased | 62 | 8 | 77 | 28
Neutrophils decreased | 56 | 26 | 65 | 37
Platelets decreased | 55 | 1.7 | 75 | 7
Hepatic
Alkaline phosphatase increased | 45 | 2.9 | 35 | 2.7
Alanine aminotransferase increased | 40 | 2.6 | 56 | 4.6
Aspartate aminotransferase increased | 38 | 2 | 49 | 2.4
Metabolic
Potassium decreased | 62 | 22 | 29 | 8
Sodium increased | 11 | 0 | 5 | 0.3
Potassium increased | 8 | 0.6 | 21 | 3

In Combination with Fluorouracil and Leucovorin after Progresssion on Gemcitabine or Gemcitabine-based Therapy

The safety data described below are derived from patients with metastatic pancreatic adenocarcinoma previously treated with gemcitabine-based therapy who received any part of protocol-specified therapy in NAPOLI-1, an international, randomized, active-controlled, open-label trial. Protocol-specified therapy consisted of ONIVYDE 70 mg/m^2 with leucovorin 400 mg/m^2 and fluorouracil 2400 mg/m^2 over 46 hours every 2 weeks (ONIVYDE/FU/LV; N=117), ONIVYDE 100 mg/m^2 every 3 weeks (N=147), or leucovorin 200 mg/m^2 and fluorouracil 2000 mg/m^2 over 24 hours weekly for 4 weeks followed by 2 week rest (FU/LV; N=134) [see Clinical Studies (14)]. Serum bilirubin within the institutional normal range, albumin ≥ 3 g/dL, and Karnofsky Performance Status (KPS) ≥ 70 were required for study entry. The median duration of exposure was 9 weeks in the ONIVYDE/FU/LV arm, 9 weeks in the ONIVYDE monotherapy arm, and 6 weeks in the FU/LV arm.

The most common adverse reactions (≥ 20%) of ONIVYDE were diarrhea, fatigue/asthenia, vomiting, nausea, decreased appetite, stomatitis, and pyrexia. The most common, severe laboratory abnormalities (≥ 10% Grade 3 or 4) were lymphopenia and neutropenia. The most common serious adverse reactions (≥ 2%) of ONIVYDE were diarrhea, vomiting, neutropenic fever or neutropenic sepsis, nausea, pyrexia, sepsis, dehydration, septic shock, pneumonia, acute renal failure, and thrombocytopenia.

Adverse reactions led to permanent discontinuation of ONIVYDE in 11% of patients receiving ONIVYDE/FU/LV; the most frequent adverse reactions resulting in discontinuation of ONIVYDE were diarrhea, vomiting, and sepsis. Dose reductions of ONIVYDE for adverse reactions occurred in 33% of patients receiving ONIVYDE/FU/LV; the most frequent adverse reactions requiring dose reductions were neutropenia, diarrhea, nausea, and anemia. ONIVYDE was withheld or delayed for adverse reactions in 62% of patients receiving ONIVYDE/FU/LV; the most frequent adverse reactions requiring interruption or delays were neutropenia, diarrhea, fatigue, vomiting, and thrombocytopenia.

Table 5 provides the frequency and severity of adverse reactions in NAPOLI-1 that occurred with higher incidence (≥5% difference for Grades 1-4 or ≥2% difference for Grades 3-4) in patients who received ONIVYDE/FU/LV compared to patients who received FU/LV.

Table 5 Adverse Reactions with Higher Incidence (≥5% Difference for Grades 1-4 [NCI CTCAE v4.0] or ≥2% Difference for Grades 3 and 4) in the ONIVYDE/FU/LV Arm
Adverse Reaction | ONIVYDE/FU/LV N=117 |  | FU/LV N=134
 | Grades 1-4 (%) | Grades 3-4 (%) | Grades 1-4 (%) | Grades 3-4 (%)
Gastrointestinal disorders
Diarrhea | 59 | 13 | 26 | 4
Early diarrhea [Early diarrhea: onset within 24 hours of ONIVYDE administration] | 30 | 3 | 15 | 0
Late diarrhea [Late diarrhea: onset >1 day after ONIVYDE administration] | 43 | 9 | 17 | 4
Vomiting | 52 | 11 | 26 | 3
Nausea | 51 | 8 | 34 | 4
Stomatitis [Includes stomatitis, aphthous stomatitis, mouth ulceration, mucosal inflammation.] | 32 | 4 | 12 | 1
Infections and infestations | 38 | 17 | 15 | 10
Sepsis | 4 | 3 | 2 | 1
Neutropenic fever/neutropenic sepsis [Includes febrile neutropenia] | 3 | 3 | 1 | 0
Gastroenteritis | 3 | 3 | 0 | 0
Intravenous catheter-related infection | 3 | 3 | 0 | 0
General disorders and administration site conditions
Fatigue/asthenia | 56 | 21 | 43 | 10
Pyrexia | 23 | 2 | 11 | 1
Metabolism and nutrition disorders
Decreased appetite | 44 | 4 | 32 | 2
Weight loss | 17 | 2 | 7 | 0
Dehydration | 8 | 4 | 7 | 2
Skin and subcutaneous tissue disorders
Alopecia | 14 | 1 | 5 | 0

Other Adverse Reactions

Clinically relevant adverse reactions occurring in <5% of patients include:

Cholinergic Reactions: ONIVYDE can cause cholinergic reactions manifesting as rhinitis, increased salivation, flushing, bradycardia, miosis, lacrimation, diaphoresis, and intestinal hyperperistalsis with abdominal cramping and early onset diarrhea. In NAPOLI-1, Grade 1 or 2 cholinergic symptoms other than early diarrhea occurred in 12 (4.5%) ONIVYDE-treated patients. Six of these 12 patients received atropine and in 1 of the 6 patients, atropine was administered for cholinergic symptoms other than diarrhea.

Infusion Reactions: Infusion reactions, consisting of rash, urticaria, periorbital edema, or pruritus, occurring on the day of ONIVYDE administration were reported in 3% of patients receiving ONIVYDE or ONIVYDE/FU/LV.

Laboratory abnormalities that occurred with higher incidence in the ONIVYDE/FU/LV arm compared to the FU/LV arm (≥5% difference) are summarized in the following table.

Table 6 Laboratory Abnormalities with Higher Incidence (≥5% Difference) in the ONIVYDE/FU/LV Arm [NCI CTCAE v4.0, worst grade shown.] [Percent based on number of patients with a baseline and at least one post-baseline measurement.]
Laboratory abnormality | ONIVYDE/FU/LV N=117 |  | FU/LV N=134
Laboratory abnormality | Grades 1-4 (%) | Grades 3-4 (%) | Grades 1-4 (%) | Grades 3-4 (%)
Hematology
Anemia | 97 | 6 | 86 | 5
Lymphopenia | 81 | 27 | 75 | 17
Neutropenia | 52 | 20 | 6 | 2
Thrombocytopenia | 41 | 2 | 33 | 0
Hepatic
Increased alanine aminotransferase (ALT) | 51 | 6 | 37 | 1
Hypoalbuminemia | 43 | 2 | 30 | 0
Metabolic
Hypomagnesemia | 35 | 0 | 21 | 0
Hypokalemia | 32 | 2 | 19 | 2
Hypocalcemia | 32 | 1 | 20 | 0
Hypophosphatemia | 29 | 4 | 18 | 1
Hyponatremia | 27 | 5 | 12 | 3
Renal
Increased creatinine | 18 | 0 | 13 | 0

6.2 Postmarketing Experience

The following adverse reactions have been identified during post approval use of ONIVYDE. Because these reactions are reported voluntarily from a population of uncertain size, it is not always possible to reliably estimate their frequency or establish a causal relationship to drug exposure.

Immune system disorders: Hypersensitivity (including Anaphylactic reaction and Angioedema)

7 DRUG INTERACTIONS

7.1 Strong CYP3A4 Inducers

Following administration of non-liposomal irinotecan (i.e., irinotecan HCl), exposure to irinotecan or its active metabolite, SN-38, is substantially reduced in adult and pediatric patients concomitantly receiving the CYP3A4 enzyme-inducing anticonvulsants phenytoin and strong CYP3A4 inducers. Avoid the use of strong CYP3A4 inducers (e.g., rifampin, phenytoin, carbamazepine, rifabutin, rifapentine, phenobarbital, St. John's wort) if possible. Substitute non-enzyme inducing therapies at least 2 weeks prior to initiation of ONIVYDE therapy [see Clinical Pharmacology (12.3)].

7.2 Strong CYP3A4 or UGT1A1 Inhibitors

Following administration of non-liposomal irinotecan (i.e., irinotecan HCl), patients receiving concomitant ketoconazole, a CYP3A4 and UGT1A1 inhibitor, have increased exposure to irinotecan and its active metabolite SN-38. Co-administration of ONIVYDE with other inhibitors of CYP3A4 (e.g., clarithromycin, indinavir, itraconazole, lopinavir, nefazodone, nelfinavir, ritonavir, saquinavir, telaprevir, voriconazole) or UGT1A1 (e.g., atazanavir, gemfibrozil, indinavir) may increase systemic exposure to irinotecan or SN-38. Avoid the use of strong CYP3A4 or UGT1A1 inhibitors if possible. Discontinue strong CYP3A4 inhibitors at least 1 week prior to starting ONIVYDE therapy [see Clinical Pharmacology (12.3)].

8 USE IN SPECIFIC POPULATIONS

8.1 Pregnancy

Risk Summary

Based on animal data with irinotecan HCl and the mechanism of action of ONIVYDE, ONIVYDE can cause fetal harm when administered to a pregnant woman [see Clinical Pharmacology (12.1)]. There are no available data in pregnant women. Embryotoxicity and teratogenicity were observed following treatment with irinotecan HCl, at doses resulting in irinotecan exposures lower than those achieved with ONIVYDE 70 mg/m^2 in humans, administered to pregnant rats and rabbits during organogenesis [see Data]. Advise pregnant women of the potential risk to a fetus.

In the U.S. general population, the estimated background risk of major birth defects and miscarriage in clinically recognized pregnancies is 2-4% and 15-20%, respectively.

Data

Animal Data

No animal studies have been conducted to evaluate the effect of irinotecan liposome on reproduction and fetal development; however, studies have been conducted with irinotecan HCl. Irinotecan crosses the placenta of rats following intravenous administration. Intravenous administration of irinotecan at a dose of 6 mg/kg/day to rats and rabbits during the period of organogenesis resulted in increased post-implantation loss and decreased numbers of live fetuses. In separate studies in rats, this dose resulted in an irinotecan exposure of approximately 0.002 times the exposure of irinotecan based on area under the curve (AUC) in patients administered ONIVYDE at the 70 mg/m^2 dose. Administration of irinotecan HCl resulted in structural abnormalities and growth delays in rats at doses greater than 1.2 mg/kg/day (approximately 0.0002 times the clinical exposure to irinotecan in ONIVYDE based on AUC). Teratogenic effects included a variety of external, visceral, and skeletal abnormalities. Irinotecan HCl administered to rat dams for the period following organogenesis through weaning at doses of 6 mg/kg/day caused decreased learning ability and decreased female body weights in the offspring.

8.2 Lactation

Risk Summary

There is no information regarding the presence of irinotecan liposome, irinotecan, or SN-38 (an active metabolite of irinotecan) in human milk, or the effects on the breastfed infant or on milk production. Irinotecan is present in rat milk [see Data].

Because of the potential for serious adverse reactions in breastfed infants from ONIVYDE, advise a nursing woman not to breastfeed during treatment with ONIVYDE and for one month after the last dose.

Data

Radioactivity appeared in rat milk within 5 minutes of intravenous administration of radiolabeled irinotecan HCl and was concentrated up to 65-fold at 4 hours after administration relative to plasma concentrations.

8.3 Females and Males of Reproductive Potential

Contraception

Females

ONIVYDE can cause fetal harm when administered to a pregnant woman [see Use in Specific Populations (8.1)]. Advise females of reproductive potential to use effective contraception during treatment with ONIVYDE and for seven months after the last dose.

Males

Because of the potential for genotoxicity, advise males with female partners of reproductive potential to use condoms during treatment with ONIVYDE and for four months after the last dose [see Nonclinical Toxicology (13.1)].

8.4 Pediatric Use

Safety and effectiveness of ONIVYDE have not been established in pediatric patients.

8.5 Geriatric Use

Of the 634 patients who received ONIVYDE as a single agent, in combination with FU and leucovorin or in combination with oxaliplatin, FU and leucovorin in NAPOLI-1 and NAPOLI 3, 49% were ≥ 65 years old and 10% were ≥ 75 years old. No overall differences in safety and effectiveness were observed between these patients and younger patients.

10 OVERDOSAGE

There are no treatment interventions known to be effective for management of overdosage of ONIVYDE.

11 DESCRIPTION

ONIVYDE is formulated with irinotecan hydrochloride trihydrate, a topoisomerase inhibitor, into a liposomal dispersion for intravenous use. The chemical name of irinotecan hydrochloride trihydrate is (S)-4,11-diethyl-3,4,12,14-tetrahydro-4-hydroxy-3,14-dioxo1H-pyrano[3',4':6,7]-indolizino[1,2-b]quinolin-9-yl-[1,4'bipiperidine]-1'-carboxylate, monohydrochloride, trihydrate. The empirical formula is C33H38N4O6∙HCl∙3H2O and the molecular weight is 677.19 g/mole. The molecular structure is:

ONIVYDE is a sterile, white to slightly yellow opaque isotonic liposomal dispersion. Each 10 mL single-dose vial contains 43 mg irinotecan free base at a concentration of 4.3 mg/mL. The liposome is a unilamellar lipid bilayer vesicle, approximately 110 nm in diameter, which encapsulates an aqueous space containing irinotecan in a gelated or precipitated state as the sucrose octasulfate salt. The vesicle is composed of 1,2-distearoyl-sn-glycero-3-phosphocholine (DSPC) 6.81 mg/mL, cholesterol 2.22 mg/mL, and methoxy-terminated polyethylene glycol (MW 2000)-distearoylphosphatidyl ethanolamine (MPEG-2000-DSPE) 0.12 mg/mL. Each mL also contains 2-[4-(2-hydroxyethyl) piperazin-1-yl]ethanesulfonic acid (HEPES) as a buffer 4.05 mg/mL and sodium chloride as an isotonicity reagent 8.42 mg/mL.

12 CLINICAL PHARMACOLOGY

12.1 Mechanism of Action

Irinotecan liposome injection is a topoisomerase 1 inhibitor encapsulated in a lipid bilayer vesicle or liposome. Topoisomerase 1 relieves torsional strain in DNA by inducing single-strand breaks. Irinotecan and its active metabolite SN-38 bind reversibly to the topoisomerase 1-DNA complex and prevent re-ligation of the single-strand breaks, leading to exposure time-dependent double-strand DNA damage and cell death. In mice bearing human tumor xenografts, irinotecan liposome administered at irinotecan HCl-equivalent doses 5-fold lower than irinotecan HCl achieved similar intratumoral exposure of SN-38.

12.3 Pharmacokinetics

The plasma pharmacokinetics of total irinotecan and total SN-38 were evaluated in patients with cancer who received ONIVYDE, as a single agent or as part of combination chemotherapy, at doses between 35 mg/m^2 and 155 mg/m^2 and concentration proportional to dose was observed.

The pharmacokinetic parameters of total irinotecan and total SN-38 following the administration of ONIVYDE 70 mg/m^2 as a single agent or part of combination chemotherapy are presented in Table 7.

Table 7 Summary of Geometric Mean (CV) Total Irinotecan and Total SN-38
Dose (mg/m^2) | Descriptive Statistics | Total Irinotecan |  |  |  | Total SN-38
Dose (mg/m^2) |  | Cmax [µg/mL] | AUCSS [day∙µg/mL] | t1/2 [day] | V [L] | Cmax [ng/mL] | AUCSS [day∙ng/mL] | V [L]
50 | Geometric Mean | 25.1 | 37.8 | 1.93 | 3.63 | 2.09 | 12.1 | 3.46
50 | CV (%) | 18.5 | 73.6 | 14 | 33.5 | 42.1 | 46.6 | 35.5
70 | Geometric Mean | 30.8 | 50.4 | 1.87 | 4.23 | 2.64 | 14.7 | 4.06
70 | CV (%) | 19.7 | 75.3 | 26.4 | 28.1 | 64.5 | 58 | 29.4
AUCSS: Area under the plasma concentration curve at steady-state
t1/2: Terminal elimination half-life
V: Volume of distribution

Distribution

Direct measurement of irinotecan liposome showed that 95% of irinotecan remains liposome -encapsulated, and the ratios between total and encapsulated forms did not change with time from 0 to 170 hours post-dose. The mean volume of distribution is summarized in Table 7.

Plasma protein binding is <0.44% of the total irinotecan in ONIVYDE.

Elimination

Metabolism

The metabolism of irinotecan liposome has not been evaluated. Irinotecan is subject to extensive metabolic conversion by various enzyme systems, including carboxylesterases to form the active metabolite SN-38, and UGT1A1 mediating glucuronidation of SN-38 to form the inactive glucuronide metabolite SN-38G. Irinotecan can also undergo CYP3A4-mediated oxidative metabolism to several inactive oxidation products, one of which can be hydrolyzed by carboxylesterase to release SN-38. In the population PK analysis of irinotecan liposome, UGT1A1*28 7/7 homozygous status (10.6%) had no effect on SN-38 clearance compared with patients not homozygous for UGT1A1*28 7/7.

Excretion

The disposition of ONIVYDE has not been elucidated in humans. Following administration of irinotecan HCl, the urinary excretion of irinotecan is 11 to 20%; SN-38, <1%; and SN-38 glucuronide, 3%. The cumulative biliary and urinary excretion of irinotecan and its metabolites (SN-38 and SN-38 glucuronide), over a period of 48 hours following administration of irinotecan HCl in two patients, ranged from approximately 25% (100 mg/m^2) to 50% (300 mg/m^2).

Specific Populations

Age, Sex, Ethnicity, Renal and Hepatic Impairment:

The population pharmacokinetic analyses suggest that age (20 to 87 years) and BSA (1.15 to 2.88 m^2) had no clinically meaningful effect on the exposure of irinotecan and SN-38.

Irinotecan and SN-38 AUC in female patients were 28% and 32% higher, respectively, than those in male patients. Irinotecan AUC in patients of Asian ethnicity were 32% lower than that in non-Asian patients. The exposures of irinotecan and SN-38 in patients with mild or moderate renal impairment were comparable to patients with normal renal function after adjusting for BSA. The exposures of irinotecan and SN-38 in patients with mild hepatic impairment (based on NCI score) were comparable to patients with normal hepatic function. There was insufficient data in patients with severe renal impairment (CLcr < 30 mL/min) or in patients with moderate and severe hepatic impairment to assess their effects on the exposures of irinotecan and SN-38. Increased AST/ALT had no effect on irinotecan clearance; however, increased bilirubin level was associated with lower SN‑38 clearance. SN-38 AUC was increased by 32% in patients with bilirubin level of 1.14 mg/dL (95th of the overall population) compared with that of median bilirubin level of 0.44 mg/dL. No data are available in patients with bilirubin >2.8 mg/dL.

Drug Interactions

In a population pharmacokinetic analysis, the pharmacokinetics of total irinotecan and total SN-38 were not altered by the co-administration of fluorouracil/leucovorin. In Study MM‑398‑07‑02‑03 and NAPOLI-3, irinotecan AUC was decreased by 33% and SN-38 Cmax increased by 23% following co-administration with oxaliplatin.

Following administration of irinotecan HCl, dexamethasone (moderate CYP3A4 inducer) does not alter the pharmacokinetics of irinotecan.

In vitro studies indicate that irinotecan, SN-38 and another metabolite, aminopentane carboxylic acid (APC), do not inhibit cytochrome P-450 isozymes.

12.5 Pharmacogenomics

Individuals who are homozygous for the UGT1A1*28 allele are at increased risk for neutropenia from irinotecan HCl. In NAPOLI-1, patients homozygous for the UGT1A1*28 allele (N=7) initiated ONIVYDE at a reduced dose of 50 mg/m^2 in combination with FU/LV. The frequency of Grade 3 or 4 neutropenia in these patients [2 of 7 (28.6%)] was similar to the frequency in patients not homozygous for the UGT1A1*28 allele who received a starting dose of ONIVYDE of 70 mg/m^2 [30 of 110 (27.3%)]. In NAPOLI-3, patients homozygous for the UGT1A1*28 allele (N = 39) initiated ONIVYDE at the same starting dose of 50 mg/m^2 as patients not homozygous for the UGT1A1*28 allele (N = 328). The frequency of Grade 3 or 4 neutropenia was 23% in patients homozygous for the UGT1A1*28 allele and 13% in patients not homozygous for the UGT1A1*28 allele. The frequency of dose reduction of ONIVYDE due to treatment-emergent adverse effects was 59% versus 51% in patients homozygous versus non-homozygous for the UGT1A1*28 allele.

13 NONCLINICAL TOXICOLOGY

13.1 Carcinogenesis, Mutagenesis, Impairment of Fertility

No studies have been performed to assess the potential of irinotecan liposome for carcinogenicity, genotoxicity or impairment of fertility. Intravenous administration of irinotecan hydrochloride to rats once weekly for 13 weeks followed by a 91-week recovery period resulted in a significant linear trend between irinotecan HCl dosage and the incidence of combined uterine horn endometrial stromal polyps and endometrial stromal sarcomas. Irinotecan HCl was clastogenic both in vitro (chromosome aberrations in Chinese hamster ovary cells) and in vivo (micronucleus test in mice). Neither irinotecan nor its active metabolite, SN-38, was mutagenic in the in vitro Ames assay.

Dedicated fertility studies have not been performed with irinotecan liposome injection. Atrophy of male and female reproductive organs was observed in dogs receiving irinotecan liposome injection every 3 weeks at doses equal to or greater than 15 mg/kg, (approximately 3 times the clinical exposure of irinotecan following administration to ONIVYDE dosed at 70 mg/m^2) for a total of 6 doses. No significant adverse effects on fertility and general reproductive performance were observed after intravenous administration of irinotecan HCl in doses of up to 6 mg/kg/day to rats; however, atrophy of male reproductive organs was observed after multiple daily irinotecan HCl doses both in rodents at 20 mg/kg (approximately 0.007 times the clinical irinotecan exposure following ONIVYDE administration at 70 mg/m^2) and in dogs at 0.4 mg/kg (0.0007 times the clinical exposure to irinotecan following administration of ONIVYDE).

14 CLINICAL STUDIES

Pancreatic Adenocarcinoma

In Combination with Oxaliplatin, Fluorouracil and Leucovorin for First-Line Treatment of Metastatic Pancreatic Adenocarcinoma

The efficacy of ONIVYDE in combination with oxaliplatin, fluorouracil and leucovorin (NALIRIFOX) was evaluated in NAPOLI 3 (NCT04083235), a randomized, multicenter, open-label, active-controlled trial in 770 patients with metastatic pancreatic adenocarcinoma who had not previously received chemotherapy in the metastatic setting. Randomization was stratified by region, liver metastases and ECOG performance status. Patients were randomized (1:1) to receive one of the following treatment arm:

- NALIRIFOX: ONIVYDE 50 mg/m^2 as an intravenous infusion over 90 minutes, followed by oxaliplatin 60 mg/m^2 as an intravenous infusion over 120 minutes, followed by leucovorin 400 mg/m^2 intravenously over 30 minutes, followed by fluorouracil 2400 mg/m^2 intravenously over 46 hours, every 2 weeks.
- Gem+NabP: Nab-paclitaxel 125 mg/m^2 as an intravenous infusion over 35 minutes, followed by gemcitabine 1000 mg/m^2 intravenously over 30 minutes on days 1, 8 and 15 of each 28-day cycle.

Patients homozygous for the UGT1A1*28 allele initiated ONIVYDE at the same dose (50 mg/m^2 ONIVYDE). Treatment continued until RECIST v1.1 defined disease progression or unacceptable toxicity. Tumor status assessments were conducted at baseline and every 8 weeks thereafter as assessed by the investigator according to RECIST v1.1.

The main efficacy outcome measure was overall survival (OS). Additional efficacy measures were investigator-assessed progression-free survival (PFS) and objective response rate (ORR).

Baseline demographic and patient characteristics were: median age of 65 years (range: 20-85); 50% age 65 or older; 56% male; 83% White, 4.9% Asian, 2.5% Black or African American, 0.4% multiple race, 0.3% American Indian or Alaska Native; 0.1% Native Hawaiian or other Pacific Islander, 1.7% other, 7% not reported; and 82% non-Hispanic, 10% Hispanic, 8% not reported. ECOG performance status was 0 or 1 in 44% and 56% of patients, respectively; 80% had liver metastases.

NAPOLI 3 demonstrated a statistically significant improvement in OS and PFS for the NALIRIFOX arm over Gem+NabP arm as summarized in Table 8 and Figure 1.

Table 8 Efficacy Results of All Randomized Patients in NAPOLI 3
 | NALIRIFOX [NALIRIFOX= ONIVYDE+oxaliplatin/5-fluorouracil/leucovorin; Gem+NabP=gemcitabine+nab-paclitaxel; CI=confidence interval] (N=383) | Gem+NabP (N=387)
Overall Survival
Number of Deaths, n (%) | 259 (68) | 285 (74)
Median Overall Survival (months) | 11.1 | 9.2
(95% CI) | (10.0, 12.1) | (8.3, 10.6)
Hazard Ratio (95% CI) | 0.84 (0.71, 0.99)
p-value [Based on stratified log-rank test.] | 0.0403
Progression-Free Survival
Death or Progression, n (%) | 249 (65) | 259 (67)
Median Progression-Free Survival (months) | 7.4 | 5.6
(95% CI) | (6.0, 7.7) | (5.3, 5.8)
Hazard Ratio (95% CI) | 0.70 (0.59, 0.85)
P-value | 0.0001
Objective Response Rate [ORR result was not statistically significant.]
ORR (95% CI) | 41.8 (36.8, 46.9) | 36.2 (31.4, 41.2)
CR, n (%) | 1 (0.3) | 1 (0.3)
PR, n (%) | 159 (41.5) | 139 (35.9)
**Based on the stratified Cox proportional hazard model; stratified by ECOG PS (0 vs. 1), region (North America vs. East Asia vs. Rest of the world), and liver metastases (yes vs. no) per interaction web response system

Figure 1 Kaplan-Meier Curve for Overall Survival in all randomized Patients in NAPOLI 3

Previously treated metastatic pancreatic adenocarcinoma in combination with fluorouracil and leucovorin

The efficacy of ONIVYDE was evaluated in NAPOLI-1 (NCT01494506), a three-arm, randomized, open-label trial in patients with metastatic pancreatic adenocarcinoma with documented disease progression, after gemcitabine or gemcitabine-based therapy. Key eligibility criteria included Karnofsky Performance Status (KPS) ≥70, serum bilirubin within institution limits of normal, and albumin ≥3.0 g/dL. Patients were randomized to receive ONIVYDE plus fluorouracil/leucovorin (ONIVYDE/FU/LV), ONIVYDE, or fluorouracil/leucovorin (FU/LV). Randomization was stratified by ethnicity (White vs. East Asian vs. other), KPS (70-80 vs. 90-100), and baseline albumin level (≥ 4 g/dL vs. 3.0-3.9 g/dL). Patients randomized to ONIVYDE/FU/LV received ONIVYDE 70 mg/m^2 as an intravenous infusion over 90 minutes, followed by leucovorin 400 mg/m^2 intravenously over 30 minutes, followed by fluorouracil 2400 mg/m^2 intravenously over 46 hours, every 2 weeks. The ONIVYDE dose of 70 mg/m^2 is based on irinotecan free base (equivalent to 80 mg/m^2 of irinotecan as the hydrochloride trihydrate). Patients randomized to ONIVYDE as a single agent received ONIVYDE 100 mg/m^2 as an intravenous infusion over 90 minutes every 3 weeks. Patients randomized to FU/LV received leucovorin 200 mg/m^2 intravenously over 30 minutes, followed by fluorouracil 2000 mg/m^2 intravenously over 24 hours, administered on Days 1, 8, 15 and 22 of a 6-week cycle. Patients homozygous for the UGT1A1*28 allele initiated ONIVYDE at a reduced dose (50 mg/m^2 ONIVYDE, if given with FU/LV or 70 mg/m^2 ONIVYDE as a single agent). When ONIVYDE was withheld or discontinued for adverse reactions, FU was also withheld or discontinued. When the dose of ONIVYDE was reduced for adverse reactions, the dose of FU was reduced by 25%. Treatment continued until disease progression or unacceptable toxicity.

The major efficacy outcome measure was overall survival (OS) with two pair-wise comparisons: ONIVYDE versus FU/LV and ONIVYDE/FU/LV versus FU/LV. Additional efficacy outcome measures were progression-free survival (PFS) and objective response rate (ORR). Tumor status assessments were conducted at baseline and every 6 weeks thereafter. The trial was initiated as a two-arm study and amended after initiation to include a third arm (ONIVYDE/FU/LV). The comparisons between the ONIVYDE/FU/LV and the FU/LV arms are limited to patients enrolled in the FU/LV arm after this protocol amendment.

Four hundred seventeen patients were randomized to: ONIVYDE/FU/LV (N=117), ONIVYDE (N=151), or FU/LV (N=149). Baseline demographics and tumor characteristics for the 236 patients randomized to ONIVYDE/FU/LV or FU/LV (N=119) after the addition of the third arm to the study were a median age of 63 years (range 34-81 years) and with 41% ≥ 65 years of age; 58% were men; 63% were White, 30% were Asian, 3% were Black or African American, and 5% were other. Mean baseline albumin level was 3.97 g/dL, and baseline KPS was 90-100 in 53% of patients. Disease characteristics included liver metastasis (67%) and lung metastasis (31%). A total of 13% of patients received gemcitabine in the neoadjuvant/adjuvant setting only, 55% of patients had 1 prior line of therapy for metastatic disease, and 33% of patients had 2 or more prior lines of therapy for metastatic disease. All patients received prior gemcitabine (alone or in combination with another agent), 54% received prior gemcitabine in combination with another agent, and 13% received prior gemcitabine in combination with nab-paclitaxel.

NAPOLI-1 demonstrated a statistically significant improvement in overall survival for the ONIVYDE/FU/LV arm over the FU/LV arm as summarized in Table 9 and Figure 2.

There was no improvement in overall survival for the ONIVYDE arm over the FU/LV arm (hazard ratio=1.00, p-value=0.97 (two-sided log-rank test)).

Table 9 Efficacy Results from NAPOLI-1 [FU/LV=5-fluorouracil/leucovorin; CI=confidence interval]
 | ONIVYDE/FU/LV (N=117) | FU/LV (N=119)
Overall Survival
Number of Deaths, n (%) | 77 (66) | 86 (72)
Median Overall Survival (months) | 6.1 | 4.2
(95% CI) | (4.8, 8.5) | (3.3, 5.3)
Hazard Ratio (95% CI) | 0.68 (0.50, 0.93)
p-value (log-rank test) | 0.014
Progression-Free Survival
Death or Progression, n (%) | 83 (71) | 94 (79)
Median Progression-Free Survival (months) | 3.1 | 1.5
(95% CI) | (2.7, 4.2) | (1.4, 1.8)
Hazard Ratio (95% CI) | 0.55 (0.41, 0.75)
Objective Response Rate
Confirmed Complete or Partial Response n (%) | 9 (7.7%) | 1 (0.8%)

Figure 2 Kaplan-Meier Curve for Overall Survival in all randomized Patients in NAPOLI-1

15 REFERENCES

1. OSHA Hazardous Drugs. OSHA. http://www.osha.gov/SLTC/hazardousdrugs/index.html

16 HOW SUPPLIED/STORAGE AND HANDLING

How Supplied

ONIVYDE is available in a single-dose vial containing 43 mg irinotecan free base at a concentration of 4.3 mg/mL.

NDC: 15054-0043-1

Storage and Handling

Store ONIVYDE at 2ºC to 8ºC (36°F to 46°F). Do NOT freeze. Protect from light.

ONIVYDE is a hazardous drug. Follow applicable special handling and disposal procedures.^1

17 PATIENT COUNSELING INFORMATION

Advise patients of the following:

Severe Neutropenia

Advise patients of the risk of neutropenia leading to severe and life-threatening infections and the need for monitoring of blood counts. Instruct patients to contact their healthcare provider immediately if experiencing signs of infection, such as fever, chills, dizziness, or shortness of breath [see Warnings and Precautions (5.1)].

Severe Diarrhea

Inform patients of the risk of severe and life-threatening diarrhea. Advise patients to stop lactose-containing products, maintain hydration, and eat frequent small meals with a low-fat diet. Advise patients to contact their healthcare provider if they experience persistent vomiting or diarrhea; black or bloody stools; or symptoms of dehydration such as lightheadedness, dizziness, or faintness [see Warnings and Precautions (5.2)].

Interstitial Lung Disease

Inform patients of the potential risk of ILD. Advise patients to contact their healthcare provider as soon as possible for new onset cough or dyspnea [see Interstitial Lung Disease (5.3)].

Hypersensitivity to irinotecan HCl or ONIVYDE

Advise patients of the potential risk of severe hypersensitivity and that ONIVYDE is contraindicated in patients with a history of severe allergic reactions with irinotecan HCl or ONIVYDE. Instruct patients to seek immediate medical attention for signs of severe hypersensitivity reaction such as chest tightness; shortness of breath; wheezing; dizziness or faintness; or swelling of the face, eyelids, or lips [see Contraindications (4) and Warnings and Precautions (5.4)].

Females and males of reproductive potential

Embryo-fetal toxicity: Inform females of reproductive potential of the potential risk to a fetus, to use effective contraception during treatment and for seven months after the last dose, and to inform their healthcare provider of a known or suspected pregnancy [see Warnings and Precautions (5.5), Use in Specific Populations (8.1, 8.3)].

Contraception: Advise male patients with female partners of reproductive potential to use condoms during treatment with ONIVYDE and for four months after the last dose [see Females and Males of Reproductive Potential (8.3)].

Lactation

Advise women not to breastfeed during treatment with ONIVYDE and for one month after the last dose [see Use in Special Populations (8.2)].

Manufactured for:
Ipsen Biopharmaceuticals, Inc. Cambridge, MA 02142
ONIVYDE is a registered trademark of Ipsen Biopharm Ltd.

PRINCIPAL DISPLAY PANEL - 43 mg/10 mL Vial Label

NDC 15054-0043-1
Rx Only

Onivyde®
(irinotecan liposome injection)

43 mg/10 mL
(4.3 mg/mL)

For Intravenous Infusion After Dilution
Single Dose Vial
Discard Unused Portion

Liposomal Formulation
Do Not Substitute For
Irinotecan Hydrochloride

PRINCIPAL DISPLAY PANEL - 43 mg/10 mL Vial Carton

NDC 15054-0043-1
Rx Only

onivyde®
(irinotecan liposome injection)

43 mg/10 mL
(4.3 mg/mL)

For Intravenous Infusion After Dilution

Warning: Hazardous drug

Single Dose Vial
Discard Unused Portion

Liposomal Formulation
Do Not Substitute For Irinotecan Hydrochloride